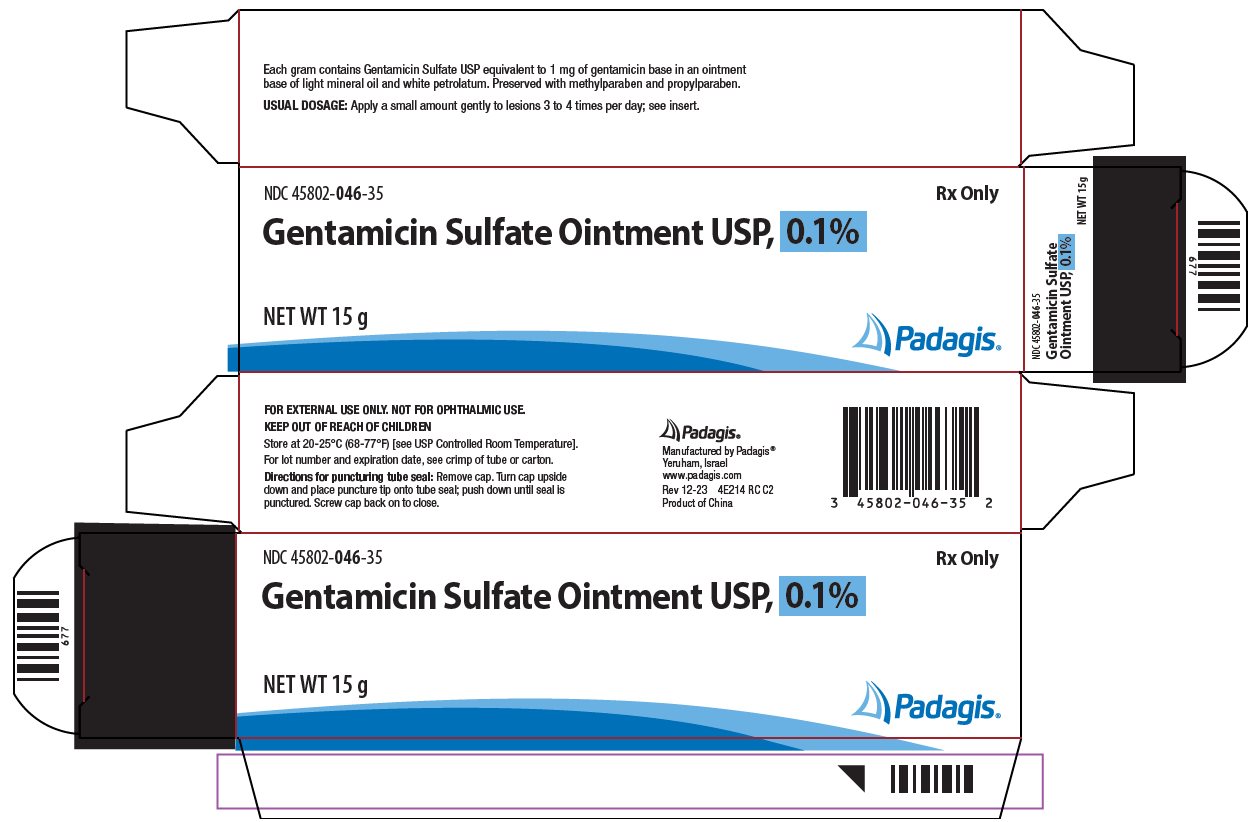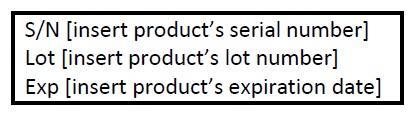 DRUG LABEL: Gentamicin Sulfate
NDC: 45802-046 | Form: OINTMENT
Manufacturer: Padagis Israel Pharmaceuticals Ltd
Category: prescription | Type: HUMAN PRESCRIPTION DRUG LABEL
Date: 20240115

ACTIVE INGREDIENTS: GENTAMICIN SULFATE 1 mg/1 g
INACTIVE INGREDIENTS: LIGHT MINERAL OIL; PETROLATUM; METHYLPARABEN; PROPYLPARABEN

Gentamicin Sulfate Ointment USP, 0.1%

For Dermatologic Use Only

Not For Ophthalmic Use

Rx Only

DESCRIPTION

Gentamicin Sulfate Ointment USP, 0.1% is a wide spectrum antibiotic preparation for topical administration. Each gram of Gentamicin Sulfate Ointment USP, 0.1% contains Gentamicin Sulfate USP equivalent to 1 mg of gentamicin base in a base of light mineral oil and white petrolatum, with 0.5 mg methylparaben and 0.1 mg propylparaben as preservatives.

CLINICAL PHARMACOLOGY

Gentamicin Sulfate is a wide spectrum antibiotic that provides highly effective topical treatment in primary and secondary bacterial infections of the skin. This product may clear infections that have not responded to other topical antibiotic agents. In impetigo contagiosa and other primary skin infections, treatment with a small amount of Gentamicin Sulfate Ointment three to four times daily usually clears the lesions promptly. In secondary skin infections, the product facilitates the treatment of the underlying dermatosis by controlling the infection. Bacteria susceptible to the action of Gentamicin Sulfate include sensitive strains of Streptococci (group A beta-hemolytic, alpha-hemolytic), Staphylococcus aureus (coagulase positive, coagulase negative, and some penicillinase-producing strains), and the gram-negative bacteria, Pseudomonas aeruginosa, Aerobacter aerogens, Escherichia coli, Proteus vulgaris and Klebsiella pneumoniae.

INDICATIONS AND USAGE

Primary skin infections: Impetigo contagiosa, superficial folliculitis, ecthyma, furunculosis, sycosis barbae, and pyoderma gangrenosum. Secondary skin infections: Infectious eczematoid dermatitis, pustular acne, pustular psoriasis, infected seborrheic dermatitis, infected contact dermatitis (including poison ivy), infected excoriations, and bacterial superinfections of fungal or viral infections. NOTE: Gentamicin Sulfate is a bactericidal agent that is not effective against viruses or fungi in skin infections. It is useful in the treatment of infected skin cysts and certain other skin abscesses when preceded by incision and drainage to permit adequate contact between the antibiotic and the infecting bacteria. Good results have been obtained in the treatment of infected stasis and other skin ulcers, infected superficial burns, paronychia, infected insect bites and stings, infected lacerations and abrasions and wounds from minor surgery. Patients sensitive to neomycin can be treated with Gentamicin Sulfate, although regular observation of patients sensitive to topical antibiotics is advisable when such patients are treated with any topical antibiotic. Gentamicin sulfate cream is recommended for wet, oozing primary infections, and greasy, secondary infections, such as postular acne or infected seborrheic dermatitis. Gentamicin Sulfate Ointment USP, 0.1% helps retain moisture and has been useful in infection on dry eczematous or psoriatic skin. Gentamicin Sulfate Ointment USP, 0.1% has been used successfully in infants over one year of age as well as in adults and children.

CONTRAINDICATIONS

Gentamicin Sulfate Ointment USP, 0.1% is contraindicated in individuals with a history of sensitivity reactions to any of its components.

PRECAUTIONS

Use of topical antibiotics occasionally allows overgrowth of nonsusceptible organisms, including fungi. If this occurs, or if irritation, sensitization, or superinfection develops, treatment with Gentamicin Sulfate Ointment USP, 0.1% should be discontinued and appropriate therapy instituted.

ADVERSE REACTIONS

In patients with dermatoses treated with Gentamicin Sulfate, irritation (erythema and pruritus) that did not usually require discontinuance of treatment has been reported in a small percentage of cases. There was no evidence of irritation or sensitization, however, in any of these patients patch-tested subsequently with gentamicin on normal skin. Possible photosensitization has been reported in several patients but could not be elicited in these patients by reapplication of gentamicin followed by exposure to ultraviolet radiation.

DOSAGE AND ADMINISTRATION

A small amount of Gentamicin Sulfate Ointment USP, 0.1% should be applied gently to lesions three to four times a day. The area treated may be covered with a gauze dressing, if desired. In impetigo contagiosa, the crusts should be removed before application of Gentamicin Sulfate Ointment USP, 0.1% to permit maximum contact between the antibiotic and the infection. Care should be exercised to avoid further contamination of the infected skin. Infected stasis ulcers have responded well to Gentamicin Sulfate under gelatin packing.

HOW SUPPLIED

Gentamicin Sulfate Ointment USP, 0.1% is available as follows:

15 g tube (NDC 45802-046-35)

30 g tube (NDC 45802-046-11)

STORAGE

Store at 20-25°C (68-77°F) [see USP Controlled Room Temperature].

Manufactured by Padagis®
Yeruham, Israel

www.padagis.com

Rev 03-23

4E200 RC PH1

Principal Display Panel - Carton

NDC 45802-046-35

Rx Only

Gentamicin Sulfate Ointment USP, 0.1%

NET WT 15 g

The following image is a placeholder representing the product identifier that is either affixed or imprinted on the drug package label during the packaging operation.